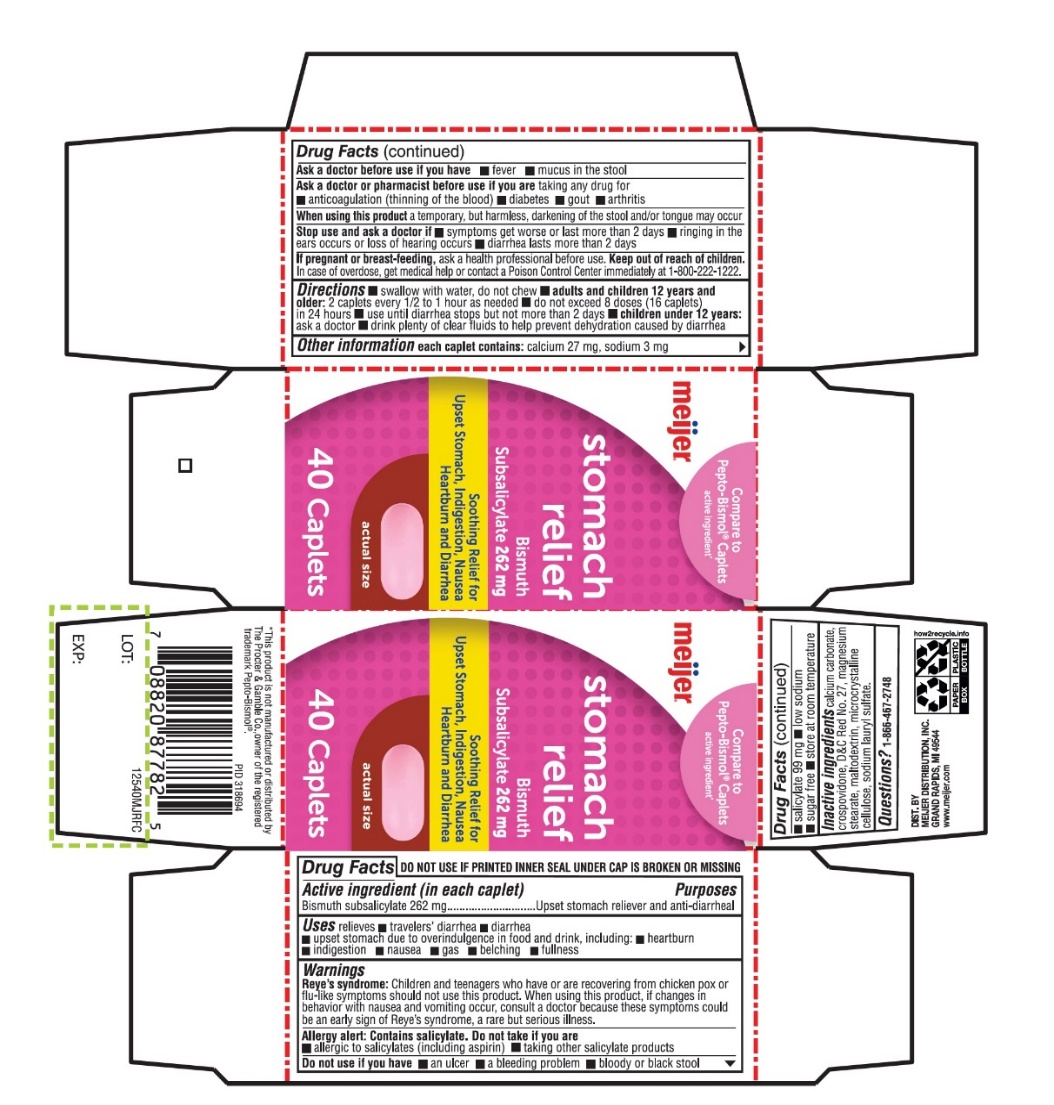 DRUG LABEL: meijer stomach relief
NDC: 41250-324 | Form: TABLET
Manufacturer: Meijer Distribution Inc
Category: otc | Type: HUMAN OTC DRUG LABEL
Date: 20251024

ACTIVE INGREDIENTS: BISMUTH SUBSALICYLATE 262 mg/1 1
INACTIVE INGREDIENTS: CALCIUM CARBONATE; CROSPOVIDONE (120 .MU.M); D&C RED NO. 27; MAGNESIUM STEARATE; MALTODEXTRIN; MICROCRYSTALLINE CELLULOSE; SODIUM LAURYL SULFATE

Meijer Stomach Relief Bismuth Subsalicylate Caplets

Active ingredient (in each caplet)

Bismuth subsalicylate 262 mg

Purpose

Upset stomach reliever and anti-diarrheal

Uses

relieves:

- travelers’ diarrhea
- diarrhea
- upset stomach due to overindulgence in food and drink, including:
- heartburn
- nausea
- gas
- belching
- fullness

Warnings

Reye's syndrome:Children and teenagers who have or are recovering from chicken pox or flu-like symptoms should not use this product. When using this product, if changes in behavior with nausea and vomiting occur, consult a doctor because these symptoms could be an early sign of Reye's syndrome, a rare but serious illness.

Allergy alert: Contains salicylate. Do not take if you are

- allergic to salicylates (including aspirin)
- taking other salicylate products

Do not use if you have

- an ulcer
- a bleeding problem
- bloody or black stool

Ask a doctor before use if you have

- fever
- mucus in the stool

Ask a doctor or pharmacist before use if you are taking any drug for

- anticoagulation (thinning of the blood)
- diabetes
- gout
- arthritis

When using this product

a temporary, but harmless, darkening of the stool and/or tongue may occur.

Stop use and ask a doctor if

- symptoms get worse or last more than 2 days
- ringing in the ears or loss of hearing occurs
- diarrhea lasts more than 2 days

If pregnant or breast-feeding,ask a health professional before use .

In case of overdose, get medical help or contact a Poison Control Center immediately at 1-800-222-1222.

Directions

- swallow with water, do not chew
- adults and children 12 years and older:2 caplets every 1/2 to 1 hour as needed
- do not exceed 8 doses (16 caplets) in 24 hours
- use until diarrhea stops but not more than 2 days
- children under 12 years:ask a doctor
- drink plenty clear fluids to help prevent dehydration caused by diarrhea.

Other information

- each caplet contains: calcium 27 mg, sodium 3 mg
- salicylate 99 mg
- low sodium
- sugar free
- store at room temperature.

TAMPER EVIDENT: DO NOT USE IF PRINTED SEAL UNDER CAP IS BROKEN OR MISSING.

Inactive ingredients

calcium carbonate, crospovidone, D&C Red No. 27, magnesium stearate, maltodextrin, microcrystalline cellulose, sodium lauryl sulfate.

Questions?

1-866-467-2748

Principal Display

meijer®

NDC# 41250-324-40

Compare To Pepto-Bismol®Caplets active ingredient*

Stomach relief

Bismuth Subsalicylate 262 mg

Soothing relief for Upset Stomach, Indigestion, Nausea, Heartburn and Diarrhea

40 caplets

OUR QUALITY GUARANTEE

WWW.MEIJER.COM/SATISFACTION

DIST. BY

MEIJER DISTRIBUTION, INC

GRAND RAPIDS, MI 49544

www.meijer.com

*This product is not manufactured or distributed by The Procter & Gamble Co., owner of the registered trademark Pepto-Bismol®.